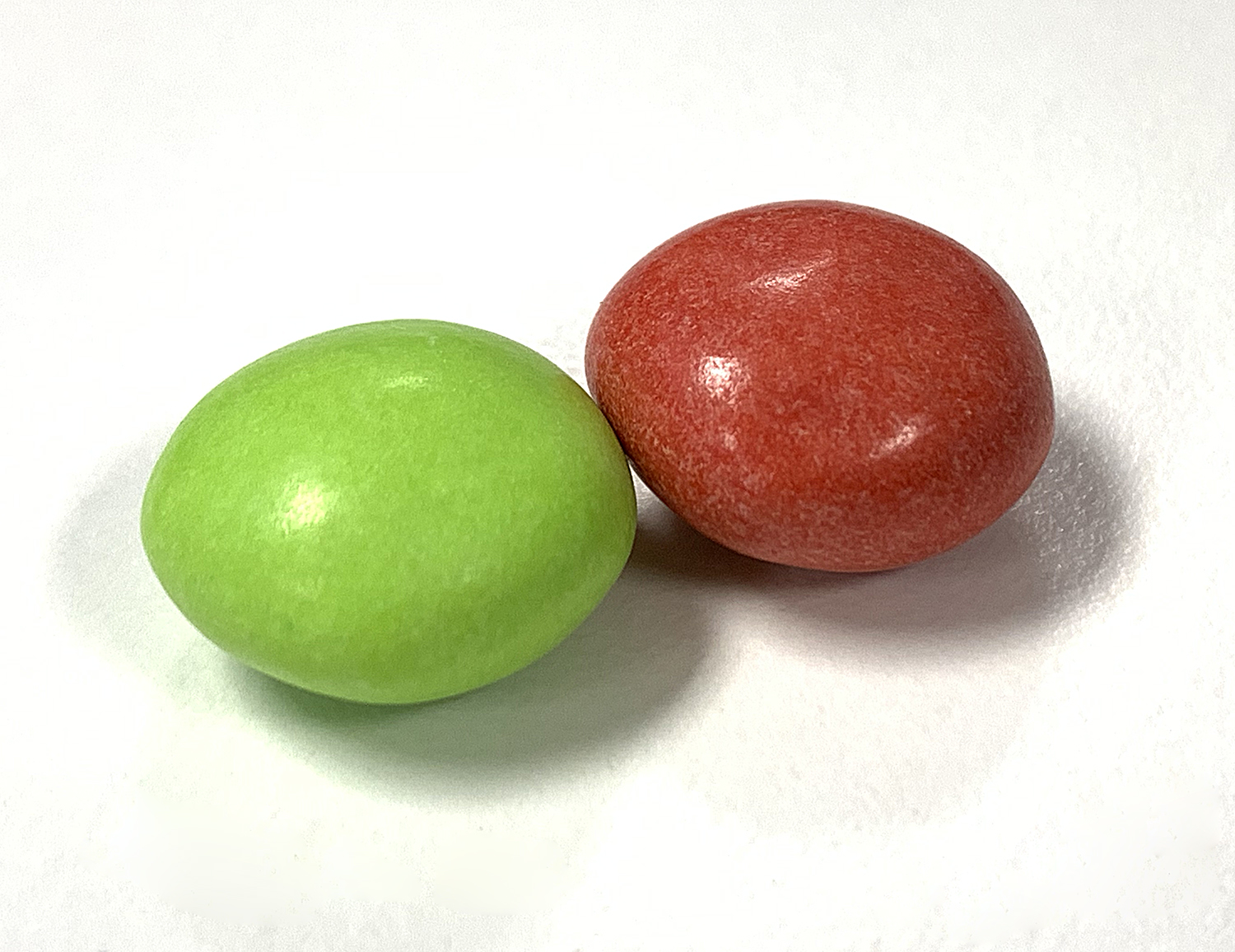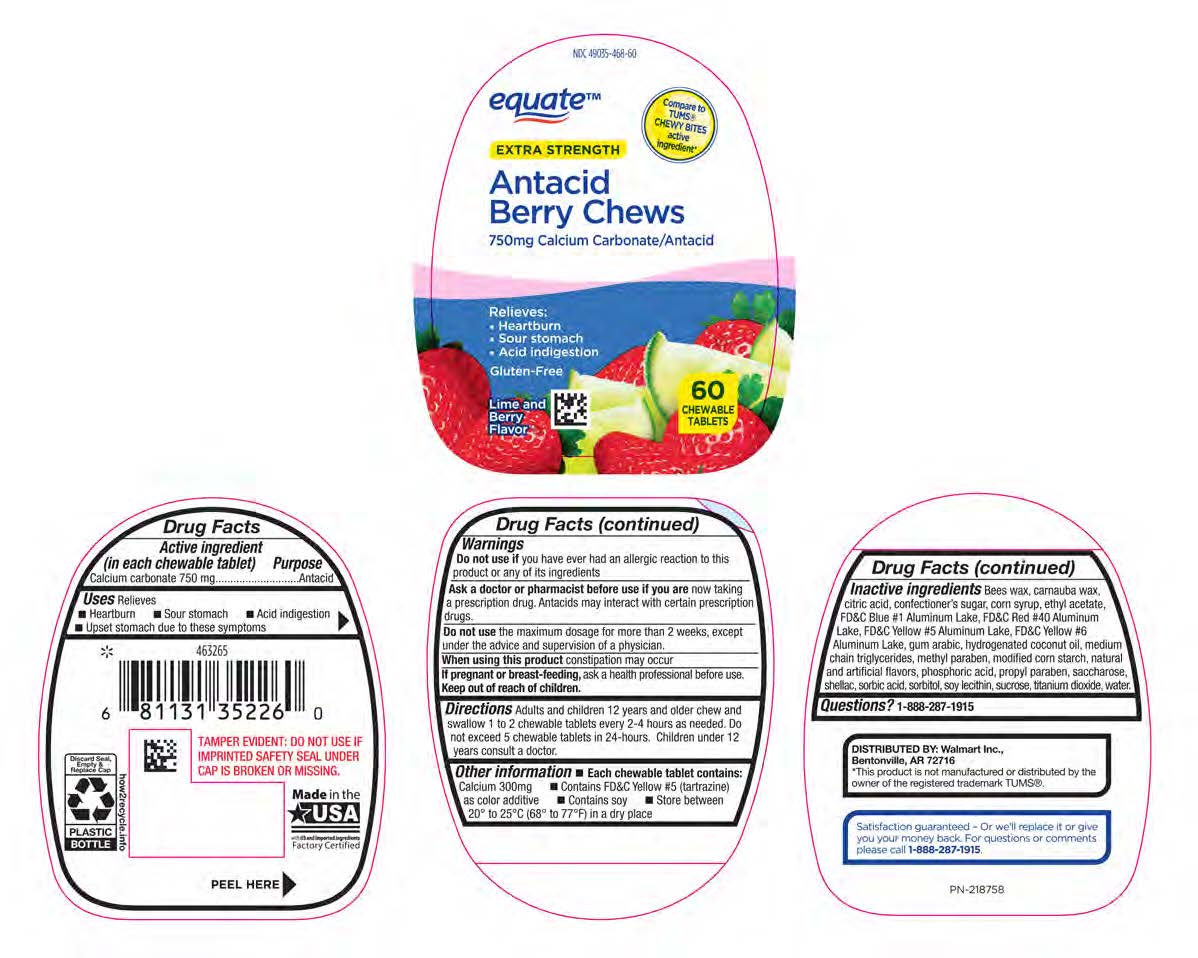 DRUG LABEL: Equate Strawberry Lime Antacid Chews
NDC: 49035-472 | Form: TABLET, CHEWABLE
Manufacturer: Walmart
Category: otc | Type: HUMAN OTC DRUG LABEL
Date: 20200116

ACTIVE INGREDIENTS: CALCIUM CARBONATE 750 mg/1 1
INACTIVE INGREDIENTS: WATER

Calcium carbonate 750 mg

Active ingredient (in each chewable tablet)

Calcium carbonate 750 mg

Purpose

Antacid

INDICATIONS AND USAGE

Uses Relieves

- Heartburn
- Sour stomach
- Acid indigestion
- Upset stomach due to these symptoms

Warnings

Do not use if you have ever had an allergic reaction to this product or any of its ingredients.

Ask a doctor or pharmacist before use if you are now taking a prescription drug. Antacids may interact with certain prescription drugs.

Do not use the maximum dosage for more than 2 weeks, except under the advice and supervision of a physician.

When using this product constipation may occur

PREGNANCY OR BREAST FEEDING

If pregnant or breast-feeding, ask a health professional before use.

Keep out of reach of children.

DOSAGE AND ADMINISTRATION

Directions: Adults and children 12 years and older chew and swallow 1 to 2 chewable tablets every 2-4 hours as needed. Do not exceed 5 chewable tablets in 24-hours. Children under 12 years consult a doctor.

Other information

- Each chewable tablet contains: Calcium 300 mg
- Contains FD&C Yellow #5 (tartrazine) as color additive
- Contains soy
- Store between 20° to 25°C (68° to 77°F) in a dry place

INACTIVE INGREDIENT

Inactive ingredients: Bees wax, carnauba wax, citric acid, confectioner's sugar, corn syrup, ethyl acetate, FD&C Blue #1 Aluminum Lake, FD&C Red #40 Aluminum Lake, FD&C Yellow #5 Aluminum Lake, FD&C Yellow #6 Aluminum Lake, gum arabic, hydrogenated coconut oil, medium chain triglycerides, methyl paraben, modified corn starch, natural and artificial flavors, phosphoric acid, propyl paraben, saccharose, shellac, sorbic acid, sorbitol, soy lecithin, sucrose, titanium dioxide, water.

Questions? 1-888-287-1915